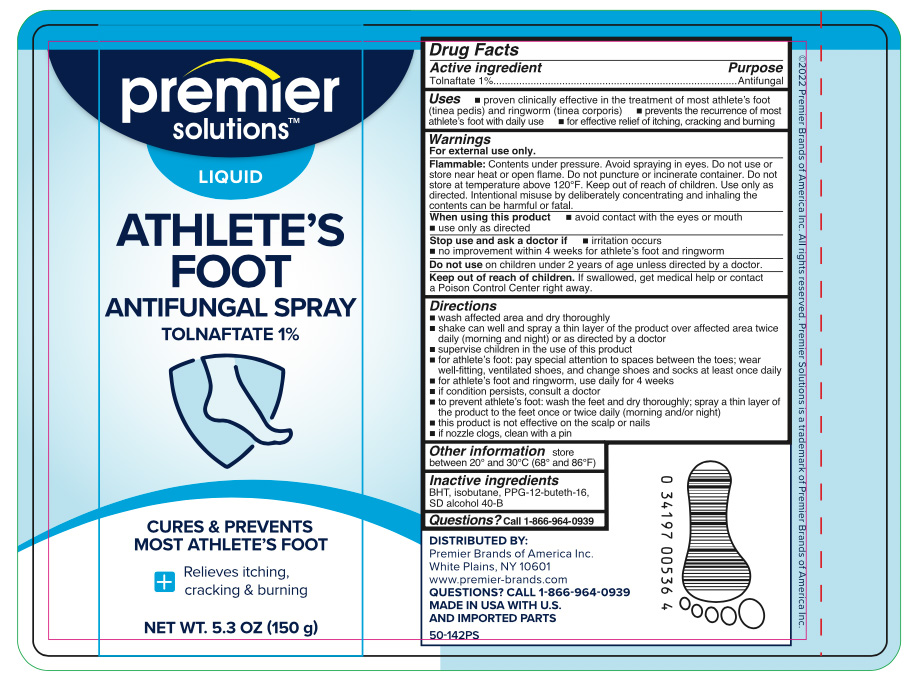 DRUG LABEL: Premier Solutions Antifungal Tolnaftate Liquid
NDC: 56104-247 | Form: AEROSOL, SPRAY
Manufacturer: Premier Brands of America, Inc.
Category: otc | Type: HUMAN OTC DRUG LABEL
Date: 20251103

ACTIVE INGREDIENTS: TOLNAFTATE 0.15 g/150 g
INACTIVE INGREDIENTS: ALCOHOL; BUTYLATED HYDROXYTOLUENE; ISOBUTANE; PPG-12-BUTETH-16

Premier Solutions Antifungal Spray Liquid

Active ingredient

Tolnaftate 1%

Purpose

Antifungal

Uses

- proven clinically effective in the treatment of athlete's foot (tinea pedis) and ringworm (tinea corporis)
- prevents the recurrence of most athlete's foot with daily use
- for effective relief of itching, cracking and burning

Warnings

For external use only.

Flammable:

Contents under pressure. Avoid spraying in eyes. Do not use or store near heat or open flame. Do not puncture or incinerate.

Do not store at temperature above 120ºF. Keep out of reach of children. Use only as directed. Intentional misuse by deliberately concentrating and inhaling contents can be harmful or fatal.

When using this product

- avoid contact with the eyes or mouth
- use only as directed

Stop use and ask a doctor if

- irritation occurs
- no improvement within 4 weeks for athlete's foot and ringworm

Keep out of reach of children.

If swallowed, get medical help or contact a Poison Control Center right away.

Directions

- wash affected area and dry thoroughly
- shake can well and spray a thin layer over affected area twice daily (morning and night) or as directed by a doctor
- supervise children in the use of this product
- for athlete's foot: pay special attention to spaces between the toes; wear well-fitting, ventilated shoes, and change shoes and socks at least once daily
- for athlete's foot and ringworm, use daily for 4 weeks
- if condition persists, consult a doctor
- to prevent athlete's foot, wash the feet and dry thoroughly; spray a thin layer of the product to the feet once or twice daily (morning and/or night)
- this product is not effective on the scalp or nails
- if nozzle clogs, clear with a pin

Other information

store between 20º and 30ºC (68º and 86ºF)

Inactive ingredients

BHT, isobutane, PPG-12-buteth-16, SD alcohol 40-B

Questions?

Call 1-866-964-0939

Principal Display Panel

Premier Solutions

Antifungal

Athlete's Foot

Liquid Spray

Tolnaftate 1%

Cures most athlete's foot and prevents recurrences

Relieves itching, cracking and burning

Net WT 5.3 OZ (150g)